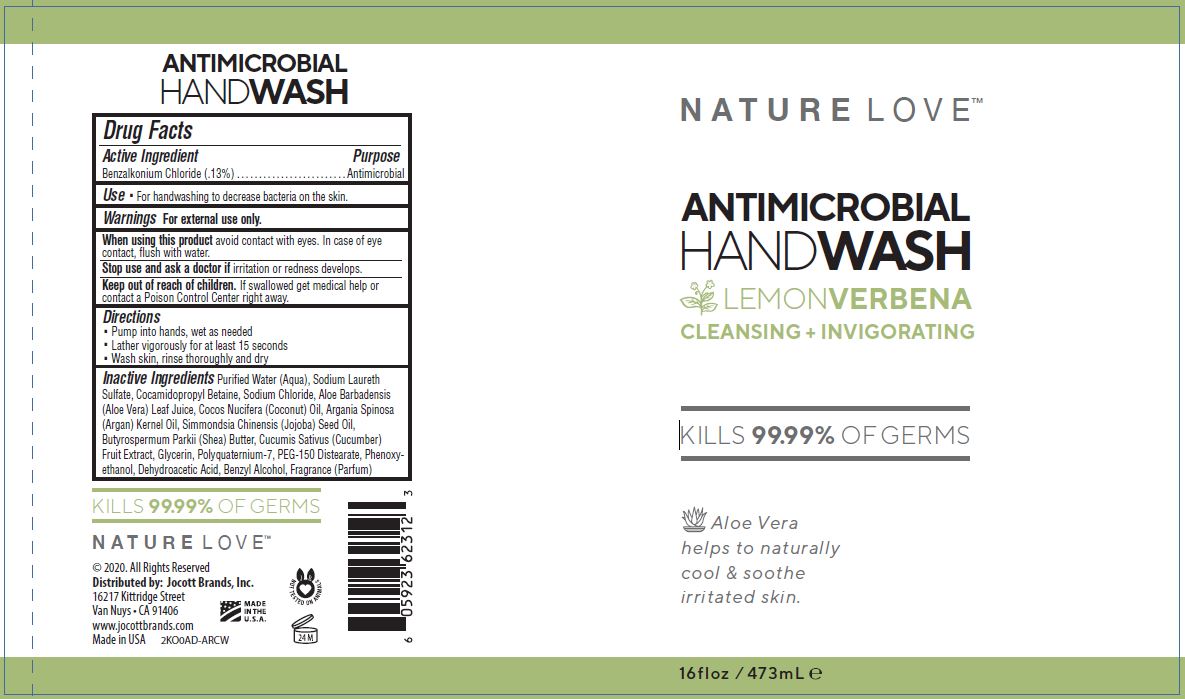 DRUG LABEL: NATURE LOVE ANTIMICROBIAL HAND WASH
NDC: 78902-109 | Form: SOAP
Manufacturer: Jocott Brands, Inc.
Category: otc | Type: HUMAN OTC DRUG LABEL
Date: 20200816

ACTIVE INGREDIENTS: BENZALKONIUM CHLORIDE 0.13 g/100 mL
INACTIVE INGREDIENTS: WATER; SODIUM LAURETH SULFATE; COCAMIDOPROPYL BETAINE; SODIUM CHLORIDE; ALOE VERA LEAF; COCONUT OIL; ARGAN OIL; JOJOBA OIL; SHEA BUTTER; CUCUMBER; GLYCERIN; POLYQUATERNIUM-7 (70/30 ACRYLAMIDE/DADMAC; 1600 KD); PEG-150 DISTEARATE; PHENOXYETHANOL; DEHYDROACETIC ACID; BENZYL ALCOHOL

NATURE LOVE ANTIMICROBIAL HAND WASH - LEMON VERBENA

ACTIVE INGREDIENT

BENZALKONIUM CHLORIDE (.13%)

PURPOSE

ANTIMICROBIAL

USE

- FOR HANDWASHING TO DECREASE BACTERIA ON THE SKIN.

WARNINGS

FOR EXTERNAL USE ONLY.

WHEN USING THIS PRODUCT AVOID CONTACT WITH EYES. IN CASE OF EYE CONTACT, FLUSH WITH WATER.

STOP USE AND ASK A DOCTOR IF IRRITATION OR REDNESS DEVELOPS.

Keep out of reach of children. If swallowed get medical help or contact a Poison Control Center right away.

DIRECTIONS

- PUMP INTO HANDS, WET AS NEEDED
- LATHER VIGOROUSLY FOR AT LEAST 15 SECONDS
- WASH SKIN, RINSE THOROUGHLY AND DRY

INACTIVE INGREDIENTS

PURIFIED WATER (AQUA), SODIUM LAURETH SULFATE, COCAMIDOPROPYL BETAINE, SODIUM CHLORIDE, ALOE BARBADENSIS (ALOE VERA) LEAF JUICE, COCOS NUCIDERA (COCONUT) OIL, ARGANIA SPINOSA (ARGAN) KERNEL OIL, SIMMONDSIA CHINENSIS (JOJOBA) SEED OIL, BUTYROSPERMUM PARKII (SHEA) BUTTER, CUCUMIS SATIVUS (CUCUMBER) FRUIT EXTRACT, GLYCERIN, POLYQUATERNIUM-7, PEG-150 DISTEARATE, PHENOXYETHANOL, DEHYDROACETIC ACID, BENZYL ALCOHOL, FRAGRANCE (PARFUM)